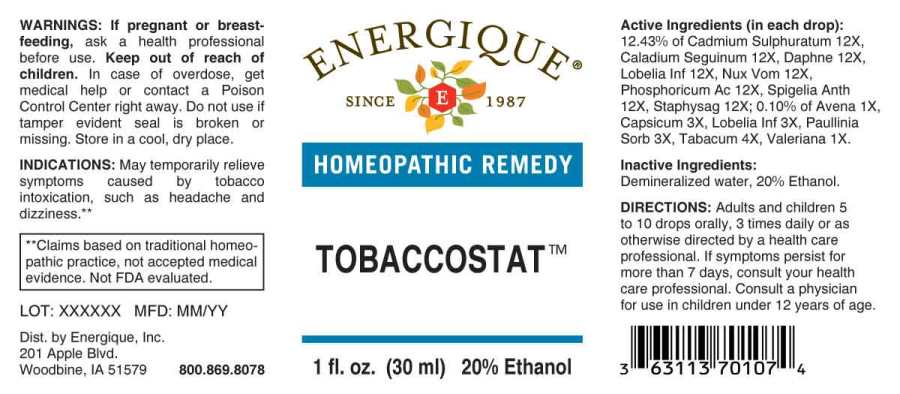 DRUG LABEL: Tobaccostat
NDC: 44911-0458 | Form: LIQUID
Manufacturer: Energique, Inc.
Category: homeopathic | Type: HUMAN OTC DRUG LABEL
Date: 20230828

ACTIVE INGREDIENTS: AVENA SATIVA FLOWERING TOP 1 [hp_X]/1 mL; VALERIAN 1 [hp_X]/1 mL; CAPSICUM 3 [hp_X]/1 mL; PAULLINIA CUPANA SEED 3 [hp_X]/1 mL; LOBELIA INFLATA WHOLE 3 [hp_X]/1 mL; TOBACCO LEAF 4 [hp_X]/1 mL; CADMIUM SULFIDE 12 [hp_X]/1 mL; DIEFFENBACHIA SEGUINE 12 [hp_X]/1 mL; DAPHNE ODORA BARK 12 [hp_X]/1 mL; STRYCHNOS NUX-VOMICA SEED 12 [hp_X]/1 mL; PHOSPHORIC ACID 12 [hp_X]/1 mL; SPIGELIA ANTHELMIA WHOLE 12 [hp_X]/1 mL
INACTIVE INGREDIENTS: WATER; ALCOHOL

DRUG FACTS:

ACTIVE INGREDIENTS:

(in each drop): 12.43% of Cadmium Sulphuratum 12X, Caladium Seguinum 12X, Daphne Indica 12X, Lobelia Inflata 12X, Nux Vomica 12X, Phosphoricum Acidum 12X, Spigelia Anthelmia 12X, Staphysagria 12X; 0.10% of Avena Sativa 1X, Capsicum Annuum 3X, Lobelia Inflata 3X, Paullinia Sorbilis 3X, Tabacum 4X,Valeriana Officinalis 1X.

INDICATIONS:

May temporarily relieve symptoms caused by tobacco intoxication, such as headache and dizziness.**

**Claims based on traditional homeopathic practice, not accepted medical evidence. Not FDA evaluated.

WARNINGS:

If pregnant or breastfeeding, ask a health professional before use.

Keep out of reach of children. In case of overdose, get medical help or contact a Poison Control Center right away.

Do not use if tamper evident seal is broken or missing.

Store in a cool, dry place.

Keep out of reach of children. In case of overdose, get medical help or contact a Poison Control Center right away.

DIRECTIONS:

Adults and children 5 to 10 drops orally, 3 times daily or as otherwise directed by a health care professional. If symptoms persist for more than 7 days, consult your health care professional. Consult a physician for use in children under 12 years of age.

INDICATIONS:

May temporarily relieve symptoms caused by tobacco intoxication, such as headache and dizziness.**

**Claims based on traditional homeopathic practice, not accepted medical evidence. Not FDA evaluated.

INACTIVE INGREDIENTS:

Demineralized water, 20% Ethanol.

QUESTIONS:

Dist. by Energique, Inc.

201 Apple Blvd.

Woodbine, IA 51579 800.869.8078

PACKAGE LABEL DISPLAY:

ENERGIQUE

SINCE 1987

HOMEOPATHIC REMEDY

TOBACCOSTAT

1 fl. oz. (30 ml)